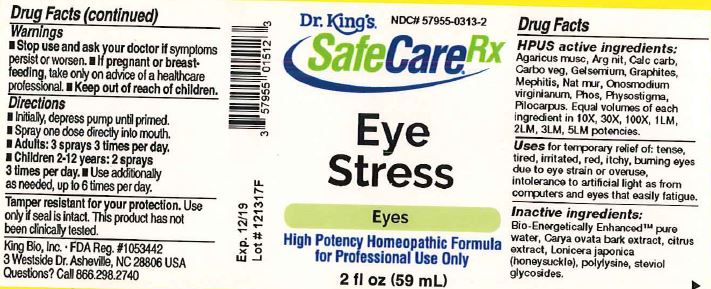 DRUG LABEL: Eye Stress
NDC: 57955-0313 | Form: LIQUID
Manufacturer: King Bio Inc.
Category: homeopathic | Type: HUMAN OTC DRUG LABEL
Date: 20180220

ACTIVE INGREDIENTS: AMANITA MUSCARIA FRUITING BODY 10 [hp_X]/59 mL; SILVER NITRATE 10 [hp_X]/59 mL; OYSTER SHELL CALCIUM CARBONATE, CRUDE 10 [hp_X]/59 mL; ACTIVATED CHARCOAL 10 [hp_X]/59 mL; GELSEMIUM SEMPERVIRENS ROOT 10 [hp_X]/59 mL; GRAPHITE 10 [hp_X]/59 mL; MEPHITIS MEPHITIS ANAL GLAND FLUID 10 [hp_X]/59 mL; SODIUM CHLORIDE 10 [hp_X]/59 mL; ONOSMODIUM VIRGINIANUM WHOLE 10 [hp_X]/59 mL; PHOSPHORUS 10 [hp_X]/59 mL; PHYSOSTIGMA VENENOSUM SEED 10 [hp_X]/59 mL; PILOCARPUS JABORANDI LEAF 10 [hp_X]/59 mL
INACTIVE INGREDIENTS: WATER; CARYA OVATA BARK; CITRUS BIOFLAVONOIDS; LONICERA JAPONICA FLOWER; POLYEPSILON-LYSINE (4000 MW); REBAUDIOSIDE A

Eye Stress™

ACTIVE INGREDIENT

Drug Facts__________________________________________________________________________________________________________

HPUS active ingredients: Agaricus musc, Arg nit, Calc carb, Carbo veg, Gelsemium, Graphites, Mephitis, Nat mur, Onosmodium, Phos, Physostigma, Pilocarpus.

Equal volumes of each ingredient in 10X, 30X, 100X, 1LM, 2LM, 3LM, 5LM potencies.

INDICATIONS AND USAGE

Uses for temporary relief of: tense, tired, irritated, red, itchy, burning eyes due to eye strain or overuse, intolerance to artificial light as from computers and eyes that easily fatigue.

Inactive Ingredients:

Bio-Energetically Enhanced™ pure water, Carya ovata bark extract, citrus extract, Lonicera japonica (honeysuckle), polylysine, steviol glycosides.

Warnings

- Stop use and ask your doctor if symptoms persist or worsen.
- If pregnant or breast-feeding, take only on advice of a healthcare professional.

- Keep out of reach of children.

Directions

- Initially, depress pump until primed.
- Spray one dose directly into mouth.
- Adults: 3 sprays 3 times per day.
- Children 2-12 years: 2 sprays 3 times per day
- Use additionally as needed, up to 6 times per day.

OTHER SAFETY INFORMATION

Tamper resistant for your protection. Use only if safety seal is intact.

PURPOSE

Uses for temporary relief of:

- tense, tired, irritated, red, itchy, burning eyes due to eye strain or overuse
- intolerance to artificial light as from computers
- eyes that easily fatigue